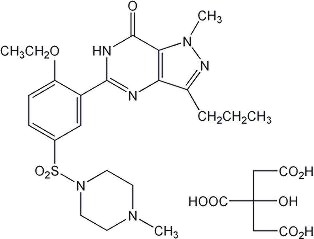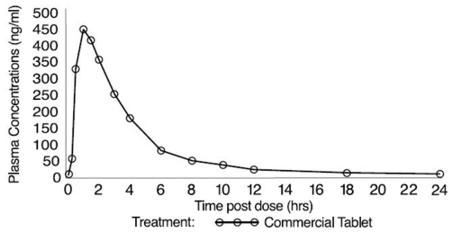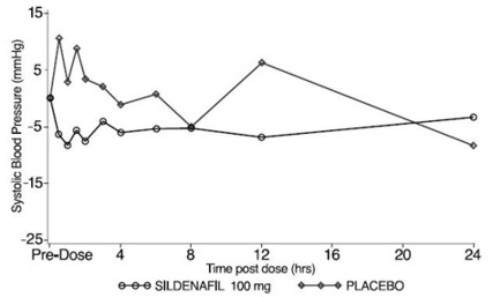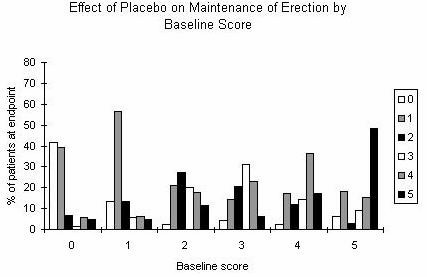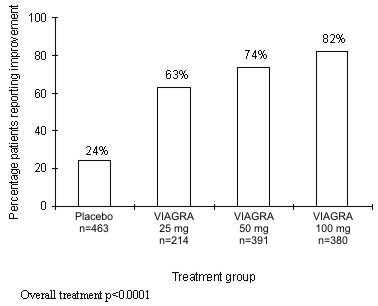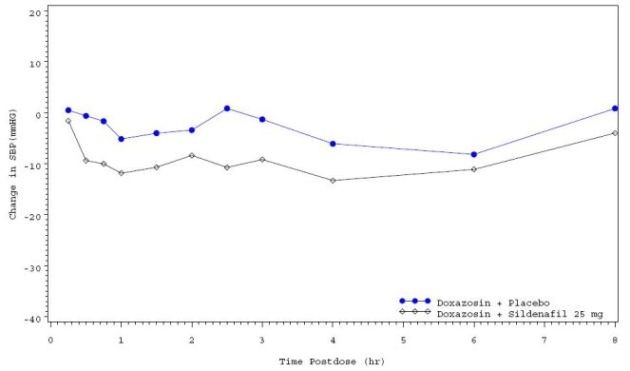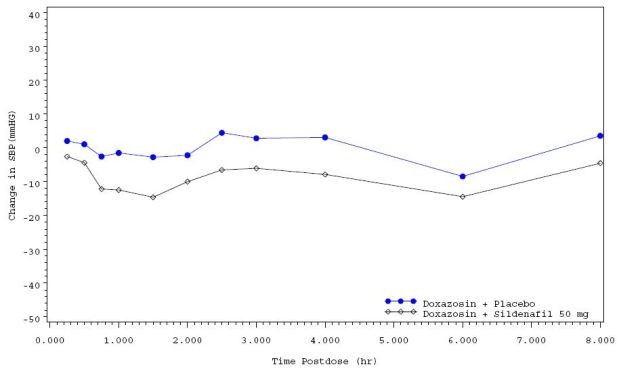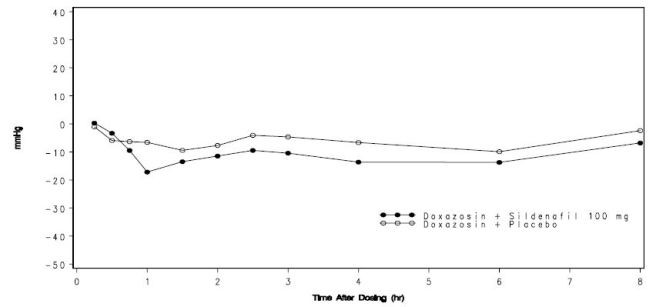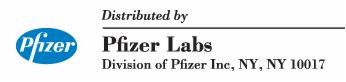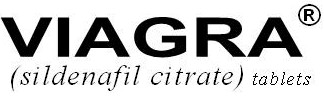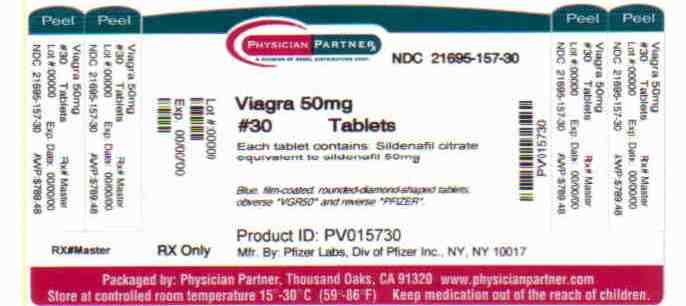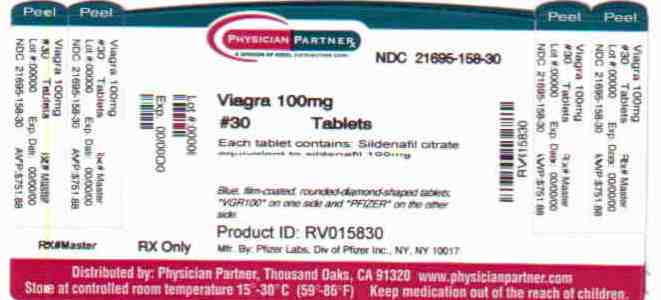 DRUG LABEL: Viagra
NDC: 21695-157 | Form: TABLET, FILM COATED
Manufacturer: Rebel Distributors Corp
Category: prescription | Type: HUMAN PRESCRIPTION DRUG LABEL
Date: 20101222

ACTIVE INGREDIENTS: SILDENAFIL CITRATE 50 mg/1 1
INACTIVE INGREDIENTS: CELLULOSE, MICROCRYSTALLINE; ANHYDROUS DIBASIC CALCIUM PHOSPHATE; CROSCARMELLOSE SODIUM; MAGNESIUM STEARATE; HYPROMELLOSES; TITANIUM DIOXIDE; LACTOSE; TRIACETIN; FD&C BLUE NO. 2; ALUMINUM OXIDE

Viagra

DESCRIPTION

VIAGRA®, an oral therapy for erectile dysfunction, is the citrate salt of sildenafil, a selective inhibitor of cyclic guanosine monophosphate (cGMP)-specific phosphodiesterase type 5 (PDE5).

Sildenafil citrate is designated chemically as 1-[[3-(6,7-dihydro-1-methyl-7-oxo-3-propyl-1

H

-pyrazolo[4,3-

d

]pyrimidin-5-yl)-4-ethoxyphenyl]sulfonyl]-4-methylpiperazine citrate and has the following structural formula:

Sildenafil citrate is a white to off-white crystalline powder with a solubility of 3.5 mg/mL in water and a molecular weight of 666.7. VIAGRA (sildenafil citrate) is formulated as blue, film-coated rounded-diamond-shaped tablets equivalent to 25 mg, 50 mg and 100 mg of sildenafil for oral administration. In addition to the active ingredient, sildenafil citrate, each tablet contains the following inactive ingredients: microcrystalline cellulose, anhydrous dibasic calcium phosphate, croscarmellose sodium, magnesium stearate, hypromellose, titanium dioxide, lactose, triacetin, and FD & C Blue #2 aluminum lake.

CLINICAL PHARMACOLOGY

Mechanism of Action

The physiologic mechanism of erection of the penis involves release of nitric oxide (NO) in the corpus cavernosum during sexual stimulation. NO then activates the enzyme guanylate cyclase, which results in increased levels of cyclic guanosine monophosphate (cGMP), producing smooth muscle relaxation in the corpus cavernosum and allowing inflow of blood. Sildenafil has no direct relaxant effect on isolated human corpus cavernosum, but enhances the effect of nitric oxide (NO) by inhibiting phosphodiesterase type 5 (PDE5), which is responsible for degradation of cGMP in the corpus cavernosum. When sexual stimulation causes local release of NO, inhibition of PDE5 by sildenafil causes increased levels of cGMP in the corpus cavernosum, resulting in smooth muscle relaxation and inflow of blood to the corpus cavernosum. Sildenafil at recommended doses has no effect in the absence of sexual stimulation.

Studies in vitro have shown that sildenafil is selective for PDE5. Its effect is more potent on PDE5 than on other known phosphodiesterases (10-fold for PDE6, >80-fold for PDE1, >700-fold for PDE2, PDE3, PDE4, PDE7, PDE8, PDE9, PDE10, and PDE11). The approximately 4,000-fold selectivity for PDE5 versus PDE3 is important because PDE3 is involved in control of cardiac contractility. Sildenafil is only about 10-fold as potent for PDE5 compared to PDE6, an enzyme found in the retina which is involved in the phototransduction pathway of the retina. This lower selectivity is thought to be the basis for abnormalities related to color vision observed with higher doses or plasma levels (see Pharmacodynamics).

In addition to human corpus cavernosum smooth muscle, PDE5 is also found in lower concentrations in other tissues including platelets, vascular and visceral smooth muscle, and skeletal muscle. The inhibition of PDE5 in these tissues by sildenafil may be the basis for the enhanced platelet antiaggregatory activity of nitric oxide observed in vitro, an inhibition of platelet thrombus formation in vivo and peripheral arterial-venous dilatation in vivo.

Pharmacokinetics and Metabolism

VIAGRA is rapidly absorbed after oral administration, with a mean absolute bioavailability of 41% (range 25–63%). Its pharmacokinetics are dose-proportional over the recommended dose range. It is eliminated predominantly by hepatic metabolism (mainly cytochrome P450 3A4) and is converted to an active metabolite with properties similar to the parent, sildenafil. The concomitant use of potent cytochrome P450 3A4 inhibitors (e.g., erythromycin, ketoconazole, itraconazole) as well as the nonspecific CYP inhibitor, cimetidine, is associated with increased plasma levels of sildenafil (see DOSAGE AND ADMINISTRATION). Both sildenafil and the metabolite have terminal half lives of about 4 hours.

Mean sildenafil plasma concentrations measured after the administration of a single oral dose of 100 mg to healthy male volunteers is depicted below:

BOXED WARNING

Figure 1: Mean Sildenafil Plasma Concentrations
in Healthy Male Volunteers.

Absorption and Distribution

VIAGRA is rapidly absorbed. Maximum observed plasma concentrations are reached within 30 to 120 minutes (median 60 minutes) of oral dosing in the fasted state. When VIAGRA is taken with a high fat meal, the rate of absorption is reduced, with a mean delay in Tmax of 60 minutes and a mean reduction in Cmax of 29%. The mean steady state volume of distribution (Vss) for sildenafil is 105 L, indicating distribution into the tissues. Sildenafil and its major circulating N-desmethyl metabolite are both approximately 96% bound to plasma proteins. Protein binding is independent of total drug concentrations.

Based upon measurements of sildenafil in semen of healthy volunteers 90 minutes after dosing, less than 0.001% of the administered dose may appear in the semen of patients.

Metabolism and Excretion

Sildenafil is cleared predominantly by the CYP3A4 (major route) and CYP2C9 (minor route) hepatic microsomal isoenzymes. The major circulating metabolite results from N-desmethylation of sildenafil, and is itself further metabolized. This metabolite has a PDE selectivity profile similar to sildenafil and an in vitro potency for PDE5 approximately 50% of the parent drug. Plasma concentrations of this metabolite are approximately 40% of those seen for sildenafil, so that the metabolite accounts for about 20% of sildenafil's pharmacologic effects.

After either oral or intravenous administration, sildenafil is excreted as metabolites predominantly in the feces (approximately 80% of administered oral dose) and to a lesser extent in the urine (approximately 13% of the administered oral dose). Similar values for pharmacokinetic parameters were seen in normal volunteers and in the patient population, using a population pharmacokinetic approach.

Pharmacokinetics in Special Populations

Geriatrics

Healthy elderly volunteers (65 years or over) had a reduced clearance of sildenafil, resulting in approximately 84% and 107% higher plasma AUC values of sildenafil and its active N-desmethyl metabolite, respectively, compared to those seen in healthy younger volunteers (18–45 years). Due to age-differences in plasma protein binding, the corresponding increase in the AUC of free (unbound) sildenafil and its active N-desmethyl metabolite were 45% and 57%, respectively.

Renal Insufficiency

In volunteers with mild (CLcr=50–80 mL/min) and moderate (CLcr=30–49 mL/min) renal impairment, the pharmacokinetics of a single oral dose of VIAGRA (50 mg) were not altered. In volunteers with severe (CLcr= less than 30 mL/min) renal impairment, sildenafil clearance was reduced, resulting in approximately doubling of AUC and Cmax compared to age-matched volunteers with no renal impairment.

In addition, N-desmethyl metabolite AUC and Cmax values significantly increased 200% and 79% respectively in subjects with severe renal impairment compared to subjects with normal renal function.

Hepatic Insufficiency

In volunteers with hepatic cirrhosis (Child-Pugh A and B), sildenafil clearance was reduced, resulting in increases in AUC (85%) and Cmax (47%) compared to age-matched volunteers with no hepatic impairment. The pharmacokinetics of sildenafil in patients with severely impaired hepatic function (Child Pugh class C) have not been studied.

Therefore, age greater than 65, hepatic impairment and severe renal impairment are associated with increased plasma levels of sildenafil. A starting oral dose of 25 mg should be considered in those patients (see DOSAGE AND ADMINISTRATION).

Pharmacodynamics

Effects of VIAGRA on Erectile Response

In eight double-blind, placebo-controlled crossover studies of patients with either organic or psychogenic erectile dysfunction, sexual stimulation resulted in improved erections, as assessed by an objective measurement of hardness and duration of erections (RigiScan®), after VIAGRA administration compared with placebo. Most studies assessed the efficacy of VIAGRA approximately 60 minutes post dose. The erectile response, as assessed by RigiScan®, generally increased with increasing sildenafil dose and plasma concentration. The time course of effect was examined in one study, showing an effect for up to 4 hours but the response was diminished compared to 2 hours.

Effects of VIAGRA on Blood Pressure

Single oral doses of sildenafil (100 mg) administered to healthy volunteers produced decreases in sitting blood pressure (mean maximum decrease in systolic/diastolic blood pressure of 8.3/5.3 mmHg). The decrease in sitting blood pressure was most notable approximately 1–2 hours after dosing, and was not different than placebo at 8 hours. Similar effects on blood pressure were noted with 25 mg, 50 mg and 100 mg of VIAGRA, therefore the effects are not related to dose or plasma levels within this dosage range. Larger effects were recorded among patients receiving concomitant nitrates (see CONTRAINDICATIONS).

BOXED WARNING

Figure 2: Mean Change from Baseline in Sitting
Systolic Blood Pressure, Healthy Volunteers.

Effects of VIAGRA on Cardiac Parameters

Single oral doses of sildenafil up to 100 mg produced no clinically relevant changes in the ECGs of normal male volunteers.

Studies have produced relevant data on the effects of VIAGRA on cardiac output. In one small, open-label, uncontrolled, pilot study, eight patients with stable ischemic heart disease underwent Swan-Ganz catheterization. A total dose of 40 mg sildenafil was administered by four intravenous infusions.

The results from this pilot study are shown in Table 1; the mean resting systolic and diastolic blood pressures decreased by 7% and 10% compared to baseline in these patients. Mean resting values for right atrial pressure, pulmonary artery pressure, pulmonary artery occluded pressure and cardiac output decreased by 28%, 28%, 20% and 7% respectively. Even though this total dosage produced plasma sildenafil concentrations which were approximately 2 to 5 times higher than the mean maximum plasma concentrations following a single oral dose of 100 mg in healthy male volunteers, the hemodynamic response to exercise was preserved in these patients.

TABLE 1. HEMODYNAMIC DATA IN PATIENTS WITH STABLE ISCHEMIC HEART DISEASE AFTER IV ADMINISTRATION OF 40 MG SILDENAFIL
Means ± SD | At rest |  |  |  | After 4 minutes of exercise
 | n | Baseline (B2) | n | Sildenafil (D1) | n | Baseline | n | Sildenafil
PAOP (mmHg) | 8 | 8.1 ± 5.1 | 8 | 6.5 ± 4.3 | 8 | 36.0 ± 13.7 | 8 | 27.8 ± 15.3
Mean PAP (mmHg) | 8 | 16.7 ± 4 | 8 | 12.1 ± 3.9 | 8 | 39.4 ± 12.9 | 8 | 31.7 ± 13.2
Mean RAP (mmHg) | 7 | 5.7 ± 3.7 | 8 | 4.1 ± 3.7 | - | - | - | -
Systolic SAP (mmHg) | 8 | 150.4 ± 12.4 | 8 | 140.6 ± 16.5 | 8 | 199.5 ± 37.4 | 8 | 187.8 ± 30.0
Diastolic SAP (mmHg) | 8 | 73.6 ± 7.8 | 8 | 65.9 ± 10 | 8 | 84.6 ± 9.7 | 8 | 79.5 ± 9.4
Cardiac output (L/min) | 8 | 5.6 ± 0.9 | 8 | 5.2 ± 1.1 | 8 | 11.5 ± 2.4 | 8 | 10.2 ± 3.5
Heart rate (bpm) | 8 | 67 ± 11.1 | 8 | 66.9 ± 12 | 8 | 101.9 ± 11.6 | 8 | 99.0 ± 20.4

In a double-blind study, 144 patients with erectile dysfunction and chronic stable angina limited by exercise, not receiving chronic oral nitrates, were randomized to a single dose of placebo or VIAGRA 100 mg 1 hour prior to exercise testing. The primary endpoint was time to limiting angina in the evaluable cohort. The mean times (adjusted for baseline) to onset of limiting angina were 423.6 and 403.7 seconds for sildenafil (N=70) and placebo, respectively. These results demonstrated that the effect of VIAGRA on the primary endpoint was statistically non-inferior to placebo.

Effects of VIAGRA on Vision

At single oral doses of 100 mg and 200 mg, transient dose-related impairment of color discrimination (blue/green) was detected using the Farnsworth-Munsell 100-hue test, with peak effects near the time of peak plasma levels. This finding is consistent with the inhibition of PDE6, which is involved in phototransduction in the retina. An evaluation of visual function at doses up to twice the maximum recommended dose revealed no effects of VIAGRA on visual acuity, intraocular pressure, or pupillometry.

Clinical Studies

In clinical studies, VIAGRA was assessed for its effect on the ability of men with erectile dysfunction (ED) to engage in sexual activity and in many cases specifically on the ability to achieve and maintain an erection sufficient for satisfactory sexual activity. VIAGRA was evaluated primarily at doses of 25 mg, 50 mg and 100 mg in 21 randomized, double-blind, placebo-controlled trials of up to 6 months in duration, using a variety of study designs (fixed dose, titration, parallel, crossover). VIAGRA was administered to more than 3,000 patients aged 19 to 87 years, with ED of various etiologies (organic, psychogenic, mixed) with a mean duration of 5 years. VIAGRA demonstrated statistically significant improvement compared to placebo in all 21 studies. The studies that established benefit demonstrated improvements in success rates for sexual intercourse compared with placebo.

The effectiveness of VIAGRA was evaluated in most studies using several assessment instruments. The primary measure in the principal studies was a sexual function questionnaire (the International Index of Erectile Function - IIEF) administered during a 4-week treatment-free run-in period, at baseline, at follow-up visits, and at the end of double-blind, placebo-controlled, at-home treatment. Two of the questions from the IIEF served as primary study endpoints; categorical responses were elicited to questions about (1) the ability to achieve erections sufficient for sexual intercourse and (2) the maintenance of erections after penetration. The patient addressed both questions at the final visit for the last 4 weeks of the study. The possible categorical responses to these questions were (0) no attempted intercourse, (1) never or almost never, (2) a few times, (3) sometimes, (4) most times, and (5) almost always or always. Also collected as part of the IIEF was information about other aspects of sexual function, including information on erectile function, orgasm, desire, satisfaction with intercourse, and overall sexual satisfaction. Sexual function data were also recorded by patients in a daily diary. In addition, patients were asked a global efficacy question and an optional partner questionnaire was administered.

The effect on one of the major end points, maintenance of erections after penetration, is shown in Figure 3, for the pooled results of 5 fixed-dose, dose-response studies of greater than one month duration, showing response according to baseline function. Results with all doses have been pooled, but scores showed greater improvement at the 50 and 100 mg doses than at 25 mg. The pattern of responses was similar for the other principal question, the ability to achieve an erection sufficient for intercourse. The titration studies, in which most patients received 100 mg, showed similar results. Figure 3 shows that regardless of the baseline levels of function, subsequent function in patients treated with VIAGRA was better than that seen in patients treated with placebo. At the same time, on-treatment function was better in treated patients who were less impaired at baseline.

BOXED WARNING

Figure 3. Effect of VIAGRA and Placebo
on Maintenance of Erection by Baseline Score.

The frequency of patients reporting improvement of erections in response to a global question in four of the randomized, double-blind, parallel, placebo-controlled fixed dose studies (1797 patients) of 12 to 24 weeks duration is shown in Figure 4. These patients had erectile dysfunction at baseline that was characterized by median categorical scores of 2 (a few times) on principal IIEF questions. Erectile dysfunction was attributed to organic (58%; generally not characterized, but including diabetes and excluding spinal cord injury), psychogenic (17%), or mixed (24%) etiologies. Sixty-three percent, 74%, and 82% of the patients on 25 mg, 50 mg and 100 mg of VIAGRA, respectively, reported an improvement in their erections, compared to 24% on placebo. In the titration studies (n=644) (with most patients eventually receiving 100 mg), results were similar.

BOXED WARNING

Figure 4. Percentage of Patients Reporting
an Improvement in Erections.

The patients in studies had varying degrees of ED. One-third to one-half of the subjects in these studies reported successful intercourse at least once during a 4-week, treatment-free run-in period.

In many of the studies, of both fixed dose and titration designs, daily diaries were kept by patients. In these studies, involving about 1600 patients, analyses of patient diaries showed no effect of VIAGRA on rates of attempted intercourse (about 2 per week), but there was clear treatment-related improvement in sexual function: per patient weekly success rates averaged 1.3 on 50–100 mg of VIAGRA vs 0.4 on placebo; similarly, group mean success rates (total successes divided by total attempts) were about 66% on VIAGRA vs about 20% on placebo.

During 3 to 6 months of double-blind treatment or longer-term (1 year), open-label studies, few patients withdrew from active treatment for any reason, including lack of effectiveness. At the end of the long-term study, 88% of patients reported that VIAGRA improved their erections.

Men with untreated ED had relatively low baseline scores for all aspects of sexual function measured (again using a 5-point scale) in the IIEF. VIAGRA improved these aspects of sexual function: frequency, firmness and maintenance of erections; frequency of orgasm; frequency and level of desire; frequency, satisfaction and enjoyment of intercourse; and overall relationship satisfaction.

One randomized, double-blind, flexible-dose, placebo-controlled study included only patients with erectile dysfunction attributed to complications of diabetes mellitus (n=268). As in the other titration studies, patients were started on 50 mg and allowed to adjust the dose up to 100 mg or down to 25 mg of VIAGRA; all patients, however, were receiving 50 mg or 100 mg at the end of the study. There were highly statistically significant improvements on the two principal IIEF questions (frequency of successful penetration during sexual activity and maintenance of erections after penetration) on VIAGRA compared to placebo. On a global improvement question, 57% of VIAGRA patients reported improved erections versus 10% on placebo. Diary data indicated that on VIAGRA, 48% of intercourse attempts were successful versus 12% on placebo.

One randomized, double-blind, placebo-controlled, crossover, flexible-dose (up to 100 mg) study of patients with erectile dysfunction resulting from spinal cord injury (n=178) was conducted. The changes from baseline in scoring on the two end point questions (frequency of successful penetration during sexual activity and maintenance of erections after penetration) were highly statistically significantly in favor of VIAGRA. On a global improvement question, 83% of patients reported improved erections on VIAGRA versus 12% on placebo. Diary data indicated that on VIAGRA, 59% of attempts at sexual intercourse were successful compared to 13% on placebo.

Across all trials, VIAGRA improved the erections of 43% of radical prostatectomy patients compared to 15% on placebo.

Subgroup analyses of responses to a global improvement question in patients with psychogenic etiology in two fixed-dose studies (total n=179) and two titration studies (total n=149) showed 84% of VIAGRA patients reported improvement in erections compared with 26% of placebo. The changes from baseline in scoring on the two end point questions (frequency of successful penetration during sexual activity and maintenance of erections after penetration) were highly statistically significantly in favor of VIAGRA. Diary data in two of the studies (n=178) showed rates of successful intercourse per attempt of 70% for VIAGRA and 29% for placebo.

A review of population subgroups demonstrated efficacy regardless of baseline severity, etiology, race and age. VIAGRA was effective in a broad range of ED patients, including those with a history of coronary artery disease, hypertension, other cardiac disease, peripheral vascular disease, diabetes mellitus, depression, coronary artery bypass graft (CABG), radical prostatectomy, transurethral resection of the prostate (TURP) and spinal cord injury, and in patients taking antidepressants/antipsychotics and antihypertensives/diuretics.

Analysis of the safety database showed no apparent difference in the side effect profile in patients taking VIAGRA with and without antihypertensive medication. This analysis was performed retrospectively, and was not powered to detect any pre-specified difference in adverse reactions.

INDICATION AND USAGE

VIAGRA is indicated for the treatment of erectile dysfunction.

CONTRAINDICATIONS

Consistent with its known effects on the nitric oxide/cGMP pathway (see CLINICAL PHARMACOLOGY), VIAGRA was shown to potentiate the hypotensive effects of nitrates, and its administration to patients who are using organic nitrates, either regularly and/or intermittently, in any form is therefore contraindicated.

After patients have taken VIAGRA, it is unknown when nitrates, if necessary, can be safely administered. Based on the pharmacokinetic profile of a single 100 mg oral dose given to healthy normal volunteers, the plasma levels of sildenafil at 24 hours post dose are approximately 2 ng/mL (compared to peak plasma levels of approximately 440 ng/mL) (see CLINICAL PHARMACOLOGY: Pharmacokinetics and Metabolism). In the following patients: age >65, hepatic impairment (e.g., cirrhosis), severe renal impairment (e.g., creatinine clearance less than 30 mL/min), and concomitant use of potent cytochrome P450 3A4 inhibitors (erythromycin), plasma levels of sildenafil at 24 hours post dose have been found to be 3 to 8 times higher than those seen in healthy volunteers. Although plasma levels of sildenafil at 24 hours post dose are much lower than at peak concentration, it is unknown whether nitrates can be safely coadministered at this time point.

VIAGRA is contraindicated in patients with a known hypersensitivity to any component of the tablet.

WARNINGS

There is a potential for cardiac risk of sexual activity in patients with preexisting cardiovascular disease. Therefore, treatments for erectile dysfunction, including VIAGRA, should not be generally used in men for whom sexual activity is inadvisable because of their underlying cardiovascular status.

VIAGRA has systemic vasodilatory properties that resulted in transient decreases in supine blood pressure in healthy volunteers (mean maximum decrease of 8.4/5.5 mmHg), (see CLINICAL PHARMACOLOGY: Pharmacodynamics). While this normally would be expected to be of little consequence in most patients, prior to prescribing VIAGRA, physicians should carefully consider whether their patients with underlying cardiovascular disease could be affected adversely by such vasodilatory effects, especially in combination with sexual activity.

Patients with the following underlying conditions can be particularly sensitive to the actions of vasodilators including VIAGRA – those with left ventricular outflow obstruction (e.g. aortic stenosis, idiopathic hypertrophic subaortic stenosis) and those with severely impaired autonomic control of blood pressure.

There is no controlled clinical data on the safety or efficacy of VIAGRA in the following groups; if prescribed, this should be done with caution.

- Patients who have suffered a myocardial infarction, stroke, or life-threatening arrhythmia within the last 6 months;
- Patients with resting hypotension (BP less than 90/50) or hypertension (BP greater than 170/110);
- Patients with cardiac failure or coronary artery disease causing unstable angina;
- Patients with retinitis pigmentosa (a minority of these patients have genetic disorders of retinal phosphodiesterases).

Prolonged erection greater than 4 hours and priapism (painful erections greater than 6 hours in duration) have been reported infrequently since market approval of VIAGRA. In the event of an erection that persists longer than 4 hours, the patient should seek immediate medical assistance. If priapism is not treated immediately, penile tissue damage and permanent loss of potency could result.

The concomitant administration of the protease inhibitor ritonavir substantially increases serum concentrations of sildenafil (11-fold increase in AUC). If VIAGRA is prescribed to patients taking ritonavir, caution should be used. Data from subjects exposed to high systemic levels of sildenafil are limited. Visual disturbances occurred more commonly at higher levels of sildenafil exposure. Decreased blood pressure, syncope, and prolonged erection were reported in some healthy volunteers exposed to high doses of sildenafil (200–800 mg). To decrease the chance of adverse events in patients taking ritonavir, a decrease in sildenafil dosage is recommended (see Drug Interactions, ADVERSE REACTIONS and DOSAGE AND ADMINISTRATION).

PRECAUTIONS

General

The evaluation of erectile dysfunction should include a determination of potential underlying causes and the identification of appropriate treatment following a complete medical assessment.

Before prescribing VIAGRA, it is important to note the following:

Caution is advised when Phosphodiesterase Type 5 (PDE5) inhibitors are co-administered with alpha-blockers. PDE5 inhibitors, including VIAGRA, and alpha-adrenergic blocking agents are both vasodilators with blood pressure lowering effects. When vasodilators are used in combination, an additive effect on blood pressure may be anticipated. In some patients, concomitant use of these two drug classes can lower blood pressure significantly (see Drug Interactions) leading to symptomatic hypotension (e.g. dizziness, lightheadedness, fainting).

Consideration should be given to the following:

- Patients should be stable on alpha-blocker therapy prior to initiating a PDE5 inhibitor. Patients who demonstrate hemodynamic instability on alpha-blocker therapy alone are at increased risk of symptomatic hypotension with concomitant use of PDE5 inhibitors. - In those patients who are stable on alpha-blocker therapy, PDE5 inhibitors should be initiated at the lowest dose. - In those patients already taking an optimized dose of a PDE5 inhibitor, alpha-blocker therapy should be initiated at the lowest dose. Stepwise increase in alpha-blocker dose may be associated with further lowering of blood pressure when taking a PDE5 inhibitor. - Safety of combined use of PDE5 inhibitors and alpha-blockers may be affected by other variables, including intravascular volume depletion and other anti-hypertensive drugs.

Viagra has systemic vasodilatory properties and may augment the blood pressure lowering effect of other anti-hypertensive medications.

Patients on multiple antihypertensive medications were included in the pivotal clinical trials for VIAGRA. In a separate drug interaction study, when amlodipine, 5 mg or 10 mg, and VIAGRA, 100 mg were orally administered concomitantly to hypertensive patients mean additional blood pressure reduction of 8 mmHg systolic and 7 mmHg diastolic were noted (see Drug Interactions).

The safety of VIAGRA is unknown in patients with bleeding disorders and patients with active peptic ulceration.

VIAGRA should be used with caution in patients with anatomical deformation of the penis (such as angulation, cavernosal fibrosis or Peyronie's disease), or in patients who have conditions which may predispose them to priapism (such as sickle cell anemia, multiple myeloma, or leukemia).

The safety and efficacy of combinations of VIAGRA with other treatments for erectile dysfunction have not been studied. Therefore, the use of such combinations is not recommended.

In humans, VIAGRA has no effect on bleeding time when taken alone or with aspirin. In vitro studies with human platelets indicate that sildenafil potentiates the antiaggregatory effect of sodium nitroprusside (a nitric oxide donor). The combination of heparin and VIAGRA had an additive effect on bleeding time in the anesthetized rabbit, but this interaction has not been studied in humans.

Information for Patients

Physicians should discuss with patients the contraindication of VIAGRA with regular and/or intermittent use of organic nitrates.

Physicians should advise patients of the potential for VIAGRA to augment the blood pressure lowering effect of alpha-blockers and anti-hypertensive medications. Concomitant administration of VIAGRA and an alpha-blocker may lead to symptomatic hypotension in some patients. Therefore, when VIAGRA is co-administered with alpha-blockers, patients should be stable on alpha-blocker therapy prior to initiating VIAGRA treatment and VIAGRA should be initiated at the lowest dose.

Physicians should discuss with patients the potential cardiac risk of sexual activity in patients with preexisting cardiovascular risk factors. Patients who experience symptoms (e.g., angina pectoris, dizziness, nausea) upon initiation of sexual activity should be advised to refrain from further activity and should discuss the episode with their physician.

Physicians should advise patients to stop use of all PDE5 inhibitors, including VIAGRA, and seek medical attention in the event of a sudden loss of vision in one or both eyes. Such an event may be a sign of non-arteritic anterior ischemic optic neuropathy (NAION), a cause of decreased vision including permanent loss of vision, that has been reported rarely post-marketing in temporal association with the use of all PDE5 inhibitors. It is not possible to determine whether these events are related directly to the use of PDE5 inhibitors or to other factors. Physicians should also discuss with patients the increased risk of NAION in individuals who have already experienced NAION in one eye, including whether such individuals could be adversely affected by use of vasodilators, such as PDE5 inhibitors (see POST-MARKETING EXPERIENCE/Special Senses).

Physicians should advise patients to stop taking PDE5 inhibitors, including VIAGRA, and seek prompt medical attention in the event of sudden decrease or loss of hearing. These events, which may be accompanied by tinnitus and dizziness, have been reported in temporal association to the intake of PDE5 inhibitors, including VIAGRA. It is not possible to determine whether these events are related directly to the use of PDE5 inhibitors or to other factors (see ADVERSE REACTIONS, CLINICAL TRIALS and POST-MARKETING EXPERIENCE).

Physicians should warn patients that prolonged erections greater than 4 hours and priapism (painful erections greater than 6 hours in duration) have been reported infrequently since market approval of VIAGRA. In the event of an erection that persists longer than 4 hours, the patient should seek immediate medical assistance. If priapism is not treated immediately, penile tissue damage and permanent loss of potency may result.

Physicians should inform patients not to take VIAGRA with other PDE5 inhibitors including REVATIO. Sildenafil is also marketed as REVATIO for the treatment of pulmonary arterial hypertension. The safety and efficacy of VIAGRA with other PDE5 inhibitors, including REVATIO, have not been studied.

The use of VIAGRA offers no protection against sexually transmitted diseases. Counseling of patients about the protective measures necessary to guard against sexually transmitted diseases, including the Human Immunodeficiency Virus (HIV), may be considered.

Drug Interactions

Effects of Other Drugs on VIAGRA

In vitro studies

Sildenafil metabolism is principally mediated by the cytochrome P450 (CYP) isoforms 3A4 (major route) and 2C9 (minor route). Therefore, inhibitors of these isoenzymes may reduce sildenafil clearance and inducers of these isoenzymes may increase sildenafil clearance.

In vivo studies

Cimetidine (800 mg), a nonspecific CYP inhibitor, caused a 56% increase in plasma sildenafil concentrations when coadministered with VIAGRA (50 mg) to healthy volunteers.

When a single 100 mg dose of VIAGRA was administered with erythromycin, a specific CYP3A4 inhibitor, at steady state (500 mg bid for 5 days), there was a 182% increase in sildenafil systemic exposure (AUC). In addition, in a study performed in healthy male volunteers, coadministration of the HIV protease inhibitor saquinavir, also a CYP3A4 inhibitor, at steady state (1200 mg tid) with VIAGRA (100 mg single dose) resulted in a 140% increase in sildenafil Cmax and a 210% increase in sildenafil AUC. VIAGRA had no effect on saquinavir pharmacokinetics. Stronger CYP3A4 inhibitors such as ketoconazole or itraconazole would be expected to have still greater effects, and population data from patients in clinical trials did indicate a reduction in sildenafil clearance when it was coadministered with CYP3A4 inhibitors (such as ketoconazole, erythromycin, or cimetidine) (see DOSAGE AND ADMINISTRATION).

In another study in healthy male volunteers, coadministration with the HIV protease inhibitor ritonavir, which is a highly potent P450 inhibitor, at steady state (500 mg bid) with VIAGRA (100 mg single dose) resulted in a 300% (4-fold) increase in sildenafil Cmax and a 1000% (11-fold) increase in sildenafil plasma AUC. At 24 hours the plasma levels of sildenafil were still approximately 200 ng/mL, compared to approximately 5 ng/mL when sildenafil was dosed alone. This is consistent with ritonavir's marked effects on a broad range of P450 substrates. VIAGRA had no effect on ritonavir pharmacokinetics (see DOSAGE AND ADMINISTRATION).

Although the interaction between other protease inhibitors and sildenafil has not been studied, their concomitant use is expected to increase sildenafil levels.

In a study of healthy male volunteers, co-administration of sildenafil at steady state (80 mg t.i.d.) with endothelin receptor antagonist bosentan (a moderate inducer of CYP3A4, CYP2C9 and possibly of cytochrome P450 2C19) at steady state (125 mg b.i.d.) resulted in a 63% decrease of sildenafil AUC and a 55% decrease in sildenafil Cmax. Concomitant administration of strong CYP3A4 inducers, such as rifampin, is expected to cause greater decreases in plasma levels of sildenafil.

Single doses of antacid (magnesium hydroxide/aluminum hydroxide) did not affect the bioavailability of VIAGRA.

Pharmacokinetic data from patients in clinical trials showed no effect on sildenafil pharmacokinetics of CYP2C9 inhibitors (such as tolbutamide, warfarin), CYP2D6 inhibitors (such as selective serotonin reuptake inhibitors, tricyclic antidepressants), thiazide and related diuretics, ACE inhibitors, and calcium channel blockers. The AUC of the active metabolite, N-desmethyl sildenafil, was increased 62% by loop and potassium-sparing diuretics and 102% by nonspecific beta-blockers. These effects on the metabolite are not expected to be of clinical consequence.

Effects of VIAGRA on Other Drugs

In vitro studies

Sildenafil is a weak inhibitor of the cytochrome P450 isoforms 1A2, 2C9, 2C19, 2D6, 2E1 and 3A4 (IC50 >150 µM). Given sildenafil peak plasma concentrations of approximately 1 µM after recommended doses, it is unlikely that VIAGRA will alter the clearance of substrates of these isoenzymes.

In vivo studies

Three double-blind, placebo-controlled, randomized, two-way crossover studies were conducted to assess the interaction of VIAGRA with doxazosin, an alpha-adrenergic blocking agent.

In the first study, a single oral dose of VIAGRA 100 mg or matching placebo was administered in a 2-period crossover design to 4 generally healthy males with benign prostatic hyperplasia (BPH). Following at least 14 consecutive daily doses of doxazosin, VIAGRA 100 mg or matching placebo was administered simultaneously with doxazosin. Following a review of the data from these first 4 subjects (details provided below), the VIAGRA dose was reduced to 25 mg. Thereafter, 17 subjects were treated with VIAGRA 25 mg or matching placebo in combination with doxazosin 4 mg (15 subjects) or doxazosin 8mg (2 subjects). The mean subject age was 66.5 years.

For the 17 subjects who received VIAGRA 25 mg and matching placebo, the placebo-subtracted mean maximum decreases from baseline (95% CI) in systolic blood pressure were as follows:

Placebo-subtracted mean maximum decrease in systolic blood pressure (mm Hg) | VIAGRA 25 mg
Supine | 7.4 (-0.9, 15.7)
Standing | 6.0 (-0.8, 12.8)

BOXED WARNING

Figure 5: Mean Standing Systolic Blood Pressure Change from Baseline

Blood pressure was measured immediately pre-dose and at 15, 30, 45 minutes, and 1, 1.5, 2, 2.5, 3, 4, 6 and 8 hours after VIAGRA or matching placebo. Outliers were defined as subjects with a standing systolic blood pressure of less than 85 mmHg or a decrease from baseline in standing systolic blood pressure of greater than 30 mmHg at one or more timepoints. There were no subjects treated with VIAGRA 25 mg who had a standing SBP less than 85mmHg. There were three subjects with a decrease from baseline in standing systolic BP greater than 30mmHg following VIAGRA 25 mg, one subject with a decrease from baseline in standing systolic BP greater than 30 mmHg following placebo and two subjects with a decrease from baseline in standing systolic BP greater than 30 mmHg following both VIAGRA and placebo. No severe adverse events potentially related to blood pressure effects were reported in this group.

Of the four subjects who received VIAGRA 100 mg in the first part of this study, a severe adverse event related to blood pressure effect was reported in one patient (postural hypotension that began 35 minutes after dosing with VIAGRA with symptoms lasting for 8 hours), and mild adverse events potentially related to blood pressure effects were reported in two others (dizziness, headache and fatigue at 1 hour after dosing; and dizziness, lightheadedness and nausea at 4 hours after dosing). There were no reports of syncope among these patients. For these four subjects, the placebo-subtracted mean maximum decreases from baseline in supine and standing systolic blood pressures were 14.8 mmHg and 21.5 mmHg, respectively. Two of these subjects had a standing SBP less than 85mmHg. Both of these subjects were protocol violators, one due to a low baseline standing SBP, and the other due to baseline orthostatic hypotension.

In the second study, a single oral dose of VIAGRA 50 mg or matching placebo was administered in a 2-period crossover design to 20 generally healthy males with BPH. Following at least 14 consecutive days of doxazosin, VIAGRA 50mg or matching placebo was administered simultaneously with doxazosin 4 mg (17 subjects) or with doxazosin 8 mg (3 subjects). The mean subject age in this study was 63.9 years.

Twenty subjects received VIAGRA 50 mg, but only 19 subjects received matching placebo. One patient discontinued the study prematurely due to an adverse event of hypotension following dosing with VIAGRA 50 mg. This patient had been taking minoxidil, a potent vasodilator, during the study.

For the 19 subjects who received both VIAGRA and matching placebo, the placebo-subtracted mean maximum decreases from baseline (95% CI) in systolic blood pressure were as follows:

Placebo-subtracted mean maximum decrease in systolic blood pressure (mm Hg) | VIAGRA 50 mg (95% CI)
Supine | 9. 8 (5.48, 12.68)
Standing | 11.62 (7.34, 15.90)

BOXED WARNING

Figure 6: Mean Standing Systolic Blood Pressure Change from Baseline

Blood pressure was measured after administration of VIAGRA at the same times as those specified for the first doxazosin study. There were two subjects who had a standing SBP of less than 85 mmHg. In these two subjects, hypotension was reported as a moderately severe adverse event, beginning at approximately 1 hour after administration of VIAGRA 50 mg and resolving after approximately 7.5 hours. There was one subject with a decrease from baseline in standing systolic BP greater than 30mmHg following VIAGRA 50 mg and one subject with a decrease from baseline in standing systolic BP greater than 30 mmHg following both VIAGRA 50 mg and placebo. There were no severe adverse events potentially related to blood pressure and no episodes of syncope reported in this study.

In the third study, a single oral dose of VIAGRA 100 mg or matching placebo was administered in a 3-period crossover design to 20 generally healthy males with BPH. In dose period 1, subjects were administered open-label doxazosin and a single dose of VIAGRA 50 mg simultaneously, after at least 14 consecutive days of doxazosin. If a subject did not successfully complete this first dosing period, he was discontinued from the study. Subjects who had successfully completed the previous doxazosin interaction study (using VIAGRA 50 mg), including no significant hemodynamic adverse events, were allowed to skip dose period 1. Treatment with doxazosin continued for at least 7 days after dose period 1. Thereafter, VIAGRA 100mg or matching placebo was administered simultaneously with doxazosin 4 mg (14 subjects) or doxazosin 8 mg (6 subjects) in standard crossover fashion. The mean subject age in this study was 66.4 years.

Twenty-five subjects were screened. Two were discontinued after study period 1: one failed to meet pre-dose screening qualifications and the other experienced symptomatic hypotension as a moderately severe adverse event 30 minutes after dosing with open-label VIAGRA 50 mg. Of the twenty subjects who were ultimately assigned to treatment, a total of 13 subjects successfully completed dose period 1, and seven had successfully completed the previous doxazosin study (using VIAGRA 50 mg).

For the 20 subjects who received VIAGRA 100 mg and matching placebo, the placebo-subtracted mean maximum decreases from baseline (95% CI) in systolic blood pressure were as follows:

Placebo-subtracted mean maximum decrease in systolic blood pressure (mm Hg) | VIAGRA 100 mg
Supine | 7.9 (4.6, 11.1)
Standing | 4.3 (-1.8, 10.3)

BOXED WARNING

Figure 7: Mean Standing Systolic Blood Pressure Change from Baseline

Blood pressure was measured after administration of VIAGRA at the same times as those specified for the previous doxazosin studies. There were three subjects who had a standing SBP of less than 85 mmHg. All three were taking VIAGRA 100 mg, and all three reported mild adverse events at the time of reductions in standing SBP, including vasodilation and lightheadedness. There were four subjects with a decrease from baseline in standing systolic BP greater than 30mmHg following VIAGRA 100 mg, one subject with a decrease from baseline in standing systolic BP greater than 30 mmHg following placebo and one subject with a decrease from baseline in standing systolic BP greater than 30 mmHg following both VIAGRA and placebo. While there were no severe adverse events potentially related to blood pressure reported in this study, one subject reported moderate vasodilatation after both VIAGRA 50 mg and 100 mg. There were no episodes of syncope reported in this study.

When VIAGRA 100 mg oral was coadministered with amlodipine, 5 mg or 10 mg oral, to hypertensive patients, the mean additional reduction on supine blood pressure was 8 mmHg systolic and 7 mmHg diastolic.

No significant interactions were shown with tolbutamide (250 mg) or warfarin (40 mg), both of which are metabolized by CYP2C9.

VIAGRA (50 mg) did not potentiate the increase in bleeding time caused by aspirin (150 mg).

VIAGRA (50 mg) did not potentiate the hypotensive effect of alcohol in healthy volunteers with mean maximum blood alcohol levels of 0.08%.

In a study of healthy male volunteers, sildenafil (100 mg) did not affect the steady state pharmacokinetics of the HIV protease inhibitors, saquinavir and ritonavir, both of which are CYP3A4 substrates.

Sildenafil at steady state (80 mg t.i.d.) resulted in a 50% increase in AUC and a 42% increase in Cmax of bosentan (125 mg b.i.d.).

Carcinogenesis, Mutagenesis, Impairment of Fertility

Sildenafil was not carcinogenic when administered to rats for 24 months at a dose resulting in total systemic drug exposure (AUCs) for unbound sildenafil and its major metabolite of 29- and 42-times, for male and female rats, respectively, the exposures observed in human males given the Maximum Recommended Human Dose (MRHD) of 100 mg. Sildenafil was not carcinogenic when administered to mice for 18–21 months at dosages up to the Maximum Tolerated Dose (MTD) of 10 mg/kg/day, approximately 0.6 times the MRHD on a mg/m^2 basis.

Sildenafil was negative in in vitro bacterial and Chinese hamster ovary cell assays to detect mutagenicity, and in vitro human lymphocytes and in vivo mouse micronucleus assays to detect clastogenicity.

There was no impairment of fertility in rats given sildenafil up to 60 mg/kg/day for 36 days to females and 102 days to males, a dose producing an AUC value of more than 25 times the human male AUC.

There was no effect on sperm motility or morphology after single 100 mg oral doses of VIAGRA in healthy volunteers.

Pregnancy, Nursing Mothers and Pediatric Use

VIAGRA is not indicated for use in newborns, children, or women.

Pregnancy Category B

No evidence of teratogenicity, embryotoxicity or fetotoxicity was observed in rats and rabbits which received up to 200 mg/kg/day during organogenesis. These doses represent, respectively, about 20 and 40 times the MRHD on a mg/m^2 basis in a 50 kg subject. In the rat pre- and postnatal development study, the no observed adverse effect dose was 30 mg/kg/day given for 36 days. In the nonpregnant rat the AUC at this dose was about 20 times human AUC. There are no adequate and well-controlled studies of sildenafil in pregnant women.

Geriatric Use

Healthy elderly volunteers (65 years or over) had a reduced clearance of sildenafil (see CLINICAL PHARMACOLOGY: Pharmacokinetics in Special Populations). Since higher plasma levels may increase both the efficacy and incidence of adverse events, a starting dose of 25 mg should be considered (see DOSAGE AND ADMINISTRATION).

ADVERSE REACTIONS

CLINICAL TRIALS

VIAGRA was administered to over 3700 patients (aged 19–87 years) during pre-marketing clinical trials worldwide. Over 550 patients were treated for longer than one year.

In placebo-controlled clinical studies, the discontinuation rate due to adverse events for VIAGRA (2.5%) was not significantly different from placebo (2.3%). The adverse events were generally transient and mild to moderate in nature.

In trials of all designs, adverse events reported by patients receiving VIAGRA were generally similar. In fixed-dose studies, the incidence of some adverse events increased with dose. The nature of the adverse events in flexible-dose studies, which more closely reflect the recommended dosage regimen, was similar to that for fixed-dose studies.

When VIAGRA was taken as recommended (on an as-needed basis) in flexible-dose, placebo-controlled clinical trials, the following adverse events were reported:

TABLE 2. ADVERSE EVENTS REPORTED BY ≥2% OF PATIENTS TREATED WITH VIAGRA AND MORE FREQUENT ON DRUG THAN PLACEBO IN PRN FLEXIBLE-DOSE PHASE II/III STUDIES
Adverse Event | Percentage of Patients VIAGRA N=734 | Reporting Event PLACEBO N=725
Headache | 16% | 4%
Flushing | 10% | 1%
Dyspepsia | 7% | 2%
Nasal Congestion | 4% | 2%
Urinary Tract Infection | 3% | 2%
Abnormal Vision* | 3% | 0%
Diarrhea | 3% | 1%
Dizziness | 2% | 1%
Rash | 2% | 1%

*

Abnormal Vision: Mild and transient, predominantly color tinge to vision, but also increased sensitivity to light or blurred vision. In these studies, only one patient discontinued due to abnormal vision.

Other adverse reactions occurred at a rate of greater than 2%, but equally common on placebo: respiratory tract infection, back pain, flu syndrome, and arthralgia.

In fixed-dose studies, dyspepsia (17%) and abnormal vision (11%) were more common at 100 mg than at lower doses. At doses above the recommended dose range, adverse events were similar to those detailed above but generally were reported more frequently.

The following events occurred in less than 2% of patients in controlled clinical trials; a causal relationship to VIAGRA is uncertain. Reported events include those with a plausible relation to drug use; omitted are minor events and reports too imprecise to be meaningful:

Body as a whole: face edema, photosensitivity reaction, shock, asthenia, pain, chills, accidental fall, abdominal pain, allergic reaction, chest pain, accidental injury.

Cardiovascular: angina pectoris, AV block, migraine, syncope, tachycardia, palpitation, hypotension, postural hypotension, myocardial ischemia, cerebral thrombosis, cardiac arrest, heart failure, abnormal electrocardiogram, cardiomyopathy.

Digestive: vomiting, glossitis, colitis, dysphagia, gastritis, gastroenteritis, esophagitis, stomatitis, dry mouth, liver function tests abnormal, rectal hemorrhage, gingivitis.

Hemic and Lymphatic: anemia and leukopenia.

Metabolic and Nutritional: thirst, edema, gout, unstable diabetes, hyperglycemia, peripheral edema, hyperuricemia, hypoglycemic reaction, hypernatremia.

Musculoskeletal: arthritis, arthrosis, myalgia, tendon rupture, tenosynovitis, bone pain, myasthenia, synovitis.

Nervous: ataxia, hypertonia, neuralgia, neuropathy, paresthesia, tremor, vertigo, depression, insomnia, somnolence, abnormal dreams, reflexes decreased, hypesthesia.

Respiratory: asthma, dyspnea, laryngitis, pharyngitis, sinusitis, bronchitis, sputum increased, cough increased.

Skin and Appendages: urticaria, herpes simplex, pruritus, sweating, skin ulcer, contact dermatitis, exfoliative dermatitis.

Special Senses: sudden decrease or loss of hearing, mydriasis, conjunctivitis, photophobia, tinnitus, eye pain, ear pain, eye hemorrhage, cataract, dry eyes.

Urogenital: cystitis, nocturia, urinary frequency, breast enlargement, urinary incontinence, abnormal ejaculation, genital edema and anorgasmia.

POST-MARKETING EXPERIENCE

Cardiovascular and cerebrovascular

Serious cardiovascular, cerebrovascular, and vascular events, including myocardial infarction, sudden cardiac death, ventricular arrhythmia, cerebrovascular hemorrhage, transient ischemic attack, hypertension, subarachnoid and intracerebral hemorrhages, and pulmonary hemorrhage have been reported post-marketing in temporal association with the use of VIAGRA. Most, but not all, of these patients had preexisting cardiovascular risk factors. Many of these events were reported to occur during or shortly after sexual activity, and a few were reported to occur shortly after the use of VIAGRA without sexual activity. Others were reported to have occurred hours to days after the use of VIAGRA and sexual activity. It is not possible to determine whether these events are related directly to VIAGRA, to sexual activity, to the patient's underlying cardiovascular disease, to a combination of these factors, or to other factors (see WARNINGS for further important cardiovascular information).

Special senses

Cases of sudden decrease or loss of hearing have been reported postmarketing in temporal association with the use of PDE5 inhibitors, including VIAGRA. In some of the cases, medical conditions and other factors were reported that may have also played a role in the otologic adverse events. In many cases, medical follow-up information was limited. It is not possible to determine whether these reported events are related directly to the use of VIAGRA, to the patient's underlying risk factors for hearing loss, a combination of these factors, or to other factors (see PRECAUTIONS, Information for Patients).

Other events

Other events reported post-marketing to have been observed in temporal association with VIAGRA and not listed in the clinical trial adverse reactions section above include:

Nervous: seizure, seizure recurrence, anxiety, and transient global amnesia.

Urogenital: prolonged erection, priapism (see WARNINGS), and hematuria.

Special Senses: diplopia, temporary vision loss/decreased vision, ocular redness or bloodshot appearance, ocular burning, ocular swelling/pressure, increased intraocular pressure, retinal vascular disease or bleeding, vitreous detachment/traction, paramacular edema and epistaxis.

Non-arteritic anterior ischemic optic neuropathy (NAION), a cause of decreased vision including permanent loss of vision, has been reported rarely post-marketing in temporal association with the use of phosphodiesterase type 5 (PDE5) inhibitors, including VIAGRA. Most, but not all, of these patients had underlying anatomic or vascular risk factors for developing NAION, including but not necessarily limited to: low cup to disc ratio ("crowded disc"), age over 50, diabetes, hypertension, coronary artery disease, hyperlipidemia and smoking. It is not possible to determine whether these events are related directly to the use of PDE5 inhibitors, to the patient's underlying vascular risk factors or anatomical defects, to a combination of these factors, or to other factors (see PRECAUTIONS/Information for Patients).

OVERDOSAGE

In studies with healthy volunteers of single doses up to 800 mg, adverse events were similar to those seen at lower doses but incidence rates and severities were increased.

In cases of overdose, standard supportive measures should be adopted as required. Renal dialysis is not expected to accelerate clearance as sildenafil is highly bound to plasma proteins and it is not eliminated in the urine.

DOSAGE AND ADMINISTRATION

For most patients, the recommended dose is 50 mg taken, as needed, approximately 1 hour before sexual activity. However, VIAGRA may be taken anywhere from 4 hours to 0.5 hour before sexual activity. Based on effectiveness and toleration, the dose may be increased to a maximum recommended dose of 100 mg or decreased to 25 mg. The maximum recommended dosing frequency is once per day.

The following factors are associated with increased plasma levels of sildenafil: age greater than 65 (40% increase in AUC), hepatic impairment (e.g., cirrhosis, 80%), severe renal impairment (creatinine clearance less than 30 mL/min, 100%), and concomitant use of potent cytochrome P450 3A4 inhibitors [ketoconazole, itraconazole, erythromycin (182%), saquinavir (210%)]. Since higher plasma levels may increase both the efficacy and incidence of adverse events, a starting dose of 25 mg should be considered in these patients.

Ritonavir greatly increased the systemic level of sildenafil in a study of healthy, non-HIV infected volunteers (11-fold increase in AUC, see Drug Interactions .) Based on these pharmacokinetic data, it is recommended not to exceed a maximum single dose of 25 mg of VIAGRA in a 48 hour period.

VIAGRA was shown to potentiate the hypotensive effects of nitrates and its administration in patients who use nitric oxide donors or nitrates in any form is therefore contraindicated.

When VIAGRA is co-administered with an alpha-blocker, patients should be stable on alpha-blocker therapy prior to initiating VIAGRA treatment and VIAGRA should be initiated at the lowest dose (see Drug Interactions).

HOW SUPPLIED

VIAGRA (sildenafil citrate) is supplied as blue, film-coated, rounded-diamond-shaped tablets containing sildenafil citrate equivalent to the nominally indicated amount of sildenafil as follows:

 | 50 mg | 100 mg
Obverse | VGR50 | VGR100
Reverse | PFIZER | PFIZER
Bottle of 15 NDC 21695-157-15 |  | NDC 548NA68-4706-0
Bottle of 30 21695-157-30 | NDC 54868-4021695-158-30 | NDC 54868-4706-5

Recommended Storage

Store at 25°C (77°F); excursions permitted to 15–30°C (59–86°F) [see USP Controlled Room Temperature].

Rx only

LAB-0221-11.0

January 2010

PATIENT SUMMARY OF INFORMATION ABOUT

This summary contains important information about VIAGRA®. It is not meant to take the place of your doctor's instructions. Read this information carefully before you start taking VIAGRA. Ask your doctor or pharmacist if you do not understand any of this information or if you want to know more about VIAGRA.

This medicine can help many men when it is used as prescribed by their doctors. However, VIAGRA is not for everyone. It is intended for use only by men who have a condition called erectile dysfunction. VIAGRA must never be used by men who are taking medicines that contain nitrates of any kind, at any time. This includes nitroglycerin. If you take VIAGRA with any nitrate medicine your blood pressure could suddenly drop to an unsafe or life threatening level.

• WHAT IS VIAGRA?

VIAGRA is a pill used to treat erectile dysfunction (impotence) in men. It can help many men who have erectile dysfunction get and keep an erection when they become sexually excited (stimulated).

You will not get an erection just by taking this medicine. VIAGRA helps a man with erectile dysfunction get an erection only when he is sexually excited.

• HOW SEX AFFECTS THE BODY

When a man is sexually excited, the penis rapidly fills with more blood than usual. The penis then expands and hardens. This is called an erection. After the man is done having sex, this extra blood flows out of the penis back into the body. The erection goes away. If an erection lasts for a long time (more than 6 hours), it can permanently damage your penis. You should call a doctor immediately if you ever have a prolonged erection that lasts more than 4 hours.

Some conditions and medicines interfere with this natural erection process. The penis cannot fill with enough blood. The man cannot have an erection. This is called erectile dysfunction if it becomes a frequent problem.

During sex, your heart works harder. Therefore sexual activity may not be advisable for people who have heart problems. Before you start any treatment for erectile dysfunction, ask your doctor if your heart is healthy enough to handle the extra strain of having sex. If you have chest pains, dizziness or nausea during sex, stop having sex and immediately tell your doctor you have had this problem.

• HOW VIAGRA WORKS

VIAGRA enables many men with erectile dysfunction to respond to sexual stimulation. When a man is sexually excited, VIAGRA helps the penis fill with enough blood to cause an erection. After sex is over, the erection goes away.

• VIAGRA IS NOT FOR EVERYONE

As noted above (How Sex Affects the Body), ask your doctor if your heart is healthy enough for sexual activity.

If you take any medicines that contain nitrates – either regularly or as needed – you should never take VIAGRA. If you take VIAGRA with any nitrate medicine or recreational drug containing nitrates, your blood pressure could suddenly drop to an unsafe level. You could get dizzy, faint, or even have a heart attack or stroke. Nitrates are found in many prescription medicines that are used to treat angina (chest pain due to heart disease) such as:

- nitroglycerin (sprays, ointments, skin patches or pastes, and tablets that are swallowed or dissolved in the mouth)
- isosorbide mononitrate and isosorbide dinitrate (tablets that are swallowed, chewed, or dissolved in the mouth)

Nitrates are also found in recreational drugs such as amyl nitrate or nitrite ("poppers"). If you are not sure if any of your medicines contain nitrates, or if you do not understand what nitrates are, ask your doctor or pharmacist.

VIAGRA is only for patients with erectile dysfunction. VIAGRA is not for newborns, children, or women. Do not let anyone else take your VIAGRA. VIAGRA must be used only under a doctor's supervision.

• WHAT VIAGRA DOES NOT DO

- VIAGRA does not cure erectile dysfunction. It is a treatment for erectile dysfunction.
- VIAGRA does not protect you or your partner from getting sexually transmitted diseases, including HIV—the virus that causes AIDS.
- VIAGRA is not a hormone or an aphrodisiac.

• WHAT TO TELL YOUR DOCTOR BEFORE YOU BEGIN VIAGRA

Only your doctor can decide if VIAGRA is right for you. VIAGRA can cause mild, temporary lowering of your blood pressure. You will need to have a thorough medical exam to diagnose your erectile dysfunction and to find out if you can safely take VIAGRA alone or with your other medicines. Your doctor should determine if your heart is healthy enough to handle the extra strain of having sex.

Be sure to tell your doctor if you:

- have ever had any heart problems (e.g., angina, chest pain, heart failure, irregular heart beats, heart attack or narrowing of the aortic valve)
- have ever had a stroke
- have low or high blood pressure
- have ever had severe vision loss
- have a rare inherited eye disease called retinitis pigmentosa
- have ever had any kidney problems
- have ever had any liver problems
- have ever had any blood problems, including sickle cell anemia or leukemia
- are allergic to sildenafil or any of the other ingredients of VIAGRA tablets
- have a deformed penis, Peyronie's disease, or ever had an erection that lasted more than 4 hours
- have stomach ulcers or any types of bleeding problems
- are taking any other medicines

• VIAGRA AND OTHER MEDICINES

Some medicines can change the way VIAGRA works. Tell your doctor about any medicines you are taking. Do not start or stop taking any medicines before checking with your doctor or pharmacist. This includes prescription and nonprescription medicines or remedies:

- Remember, VIAGRA should never be used with medicines that contain nitrates (see VIAGRA Is Not for Everyone).
- If you are taking medicines called alpha-blockers for the treatment of high blood pressure or prostate problems, your blood pressure could suddenly drop. You could get dizzy or faint.
- If you are taking a protease inhibitor, your dose may be adjusted (please see Finding the Right Dose for You).
- VIAGRA should not be used with any other medical treatments that cause erections. These treatments include pills, medicines that are injected or inserted into the penis, implants or vacuum pumps.
- VIAGRA contains sildenafil, which is the same medicine found in another drug called REVATIO. REVATIO is used to treat a rare disease called pulmonary arterial hypertension. VIAGRA should not be used with REVATIO.

• FINDING THE RIGHT DOSE FOR YOU

VIAGRA comes in different doses (25 mg, 50 mg and 100 mg). If you do not get the results you expect, talk with your doctor. You and your doctor can determine the dose that works best for you.

- Do not take more VIAGRA than your doctor prescribes.
- If you think you need a larger dose of VIAGRA, check with your doctor.
- VIAGRA should not be taken more than once a day.

Your doctor may prescribe a lower dose of VIAGRA in certain circumstances. For example:

- If you are older than age 65, or have serious liver or kidney problems, your doctor may start you at the lowest dose (25 mg) of VIAGRA.
- If you are taking protease inhibitors, such as for the treatment of HIV, your doctor may recommend a 25 mg dose and may limit you to a maximum single dose of 25 mg of VIAGRA in a 48 hour period.
- If you have prostate problems or high blood pressure for which you take medicines called alpha blockers, your doctor may start you on a lower dose of VIAGRA.

• HOW TO TAKE VIAGRA

Take VIAGRA about one hour before you plan to have sex. Beginning in about 30 minutes and for up to 4 hours, VIAGRA can help you get an erection if you are sexually excited. If you take VIAGRA after a high-fat meal (such as a cheeseburger and french fries), the medicine may take a little longer to start working. VIAGRA can help you get an erection when you are sexually excited. You will not get an erection just by taking the pill.

• POSSIBLE SIDE EFFECTS

Like all medicines, VIAGRA can cause some side effects. These effects are usually mild to moderate and usually don't last longer than a few hours. Some of these side effects are more likely to occur with higher doses. The most common side effects of VIAGRA are headache, flushing of the face, and upset stomach. Less common side effects that may occur are temporary changes in color vision (such as trouble telling the difference between blue and green objects or having a blue color tinge to them), eyes being more sensitive to light, or blurred vision.

In rare instances, men taking PDE5 inhibitors (oral erectile dysfunction medicines, including VIAGRA) reported a sudden decrease or loss of vision in one or both eyes. It is not possible to determine whether these events are related directly to these medicines, to other factors such as high blood pressure or diabetes, or to a combination of these. If you experience sudden decrease or loss of vision, stop taking PDE5 inhibitors, including VIAGRA, and call a doctor right away.

In rare instances, men have reported an erection that lasts many hours. You should call a doctor immediately if you ever have an erection that lasts more than 4 hours. If not treated right away, permanent damage to your penis could occur (see How Sex Affects the Body).

Sudden loss or decrease in hearing, sometimes with ringing in the ears and dizziness, has been rarely reported in people taking PDE5 inhibitors, including VIAGRA. It is not possible to determine whether these events are related directly to the PDE5 inhibitors, to other diseases or medications, to other factors, or to a combination of factors. If you experience these symptoms, stop taking VIAGRA and contact a doctor right away.

Heart attack, stroke, irregular heart beats, and death have been reported rarely in men taking VIAGRA. Most, but not all, of these men had heart problems before taking this medicine. It is not possible to determine whether these events were directly related to VIAGRA.

VIAGRA may cause other side effects besides those listed on this sheet. If you want more information or develop any side effects or symptoms you are concerned about, call your doctor.

• ACCIDENTAL OVERDOSE

In case of accidental overdose, call your doctor right away.

• STORING VIAGRA

Keep VIAGRA out of the reach of children. Keep VIAGRA in its original container. Store at 25°C (77°F); excursions permitted to 15–30°C (59–86°F) [see USP Controlled Room Temperature].

• FOR MORE INFORMATION ON VIAGRA

VIAGRA is a prescription medicine used to treat erectile dysfunction. Only your doctor can decide if it is right for you. This sheet is only a summary. If you have any questions or want more information about VIAGRA, talk with your doctor or pharmacist, visit www.viagra.com, or call 1-888-4VIAGRA.

LAB-0220-7.0
January 2010

Repackaged by;

Rebel Distributors Corp

Thousand Oaks, CA 91320